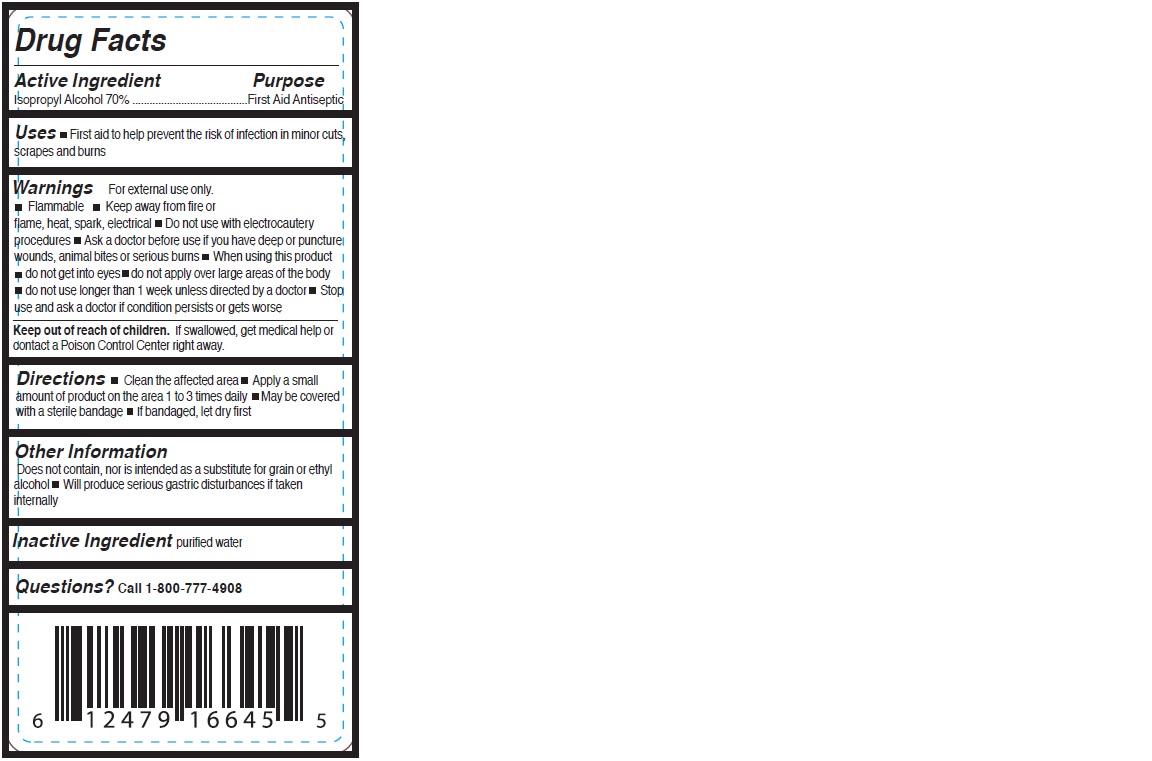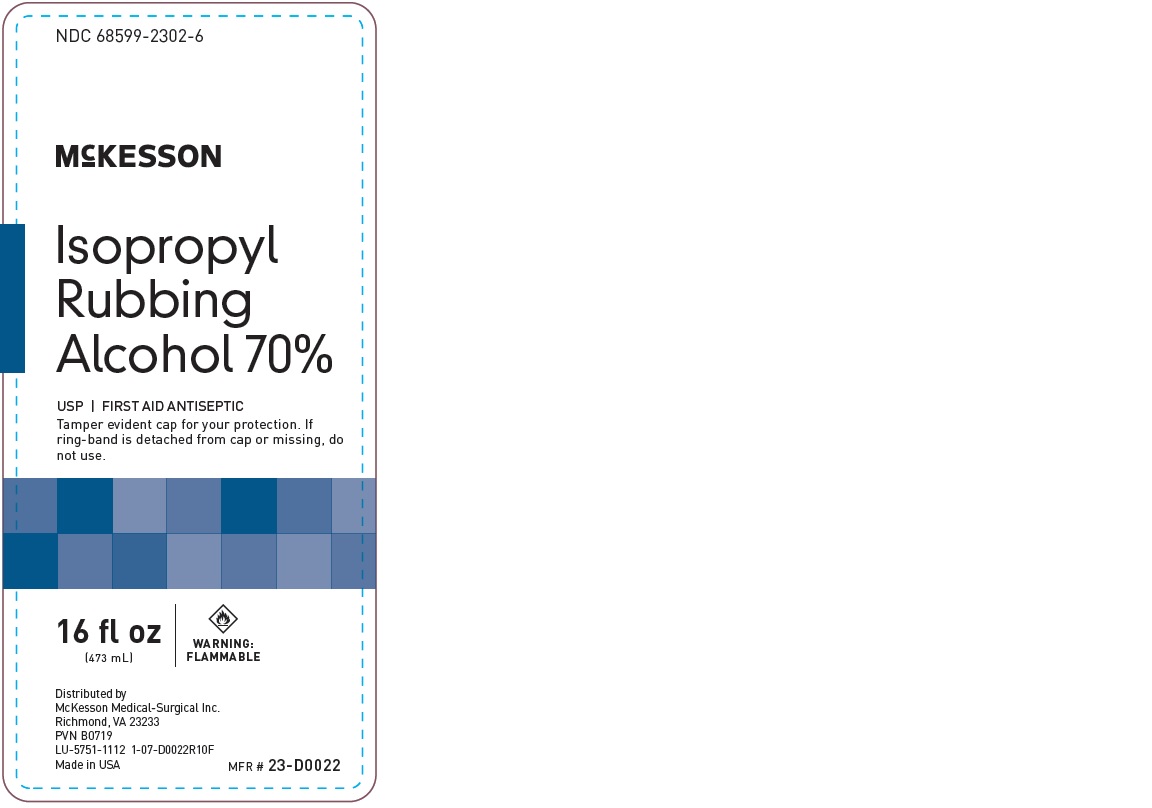 DRUG LABEL: Isopropyl Rubbing Alcohol
NDC: 68599-2302 | Form: SOLUTION
Manufacturer: McKesson Medical-Surgical Inc.
Category: otc | Type: HUMAN OTC DRUG LABEL
Date: 20241115

ACTIVE INGREDIENTS: ISOPROPYL ALCOHOL 700 mg/1 mL
INACTIVE INGREDIENTS: WATER

Isopropyl Rubbing Alcohol

Drug Facts

Active Ingredient

Isopropyl Alcohol 70%

Purpose

First Aid Antiseptic

Use

First aid to help prevent the risk of infection in minor cuts, scrapes and burns

Warnings

- For external use only
- Flammable
- Keep away from fire or flame, heat, spark, electrical

- Do not use with electrocautery procedures

- Ask a doctor before use if you have deep or puncture wounds, animal bites or serious burns

- When using this product
  - do not get into eyes
  - do not apply over large areas of the body
  - do not use longer than 1 week unless directed by a doctor

- Stop use and ask a doctor if condition persists or gets worse

- Keep out of reach of children.If swallowed, get medical help or contact a Poison Control Center right away.

Directions

- Clean the affected area
- Apply a small amount of this product 1 to 3 times daily
- May be covered with a sterile bandage
- If bandaged, let dry first

Other Information

- Does not contain, nor is intended as a substitute for grain or ethyl alcohol
- Will produce serious gastric disturbances if taken internally

Inactive Ingredient

purified water

Distributed By McKesson Medical-Surgical Inc.
Richmond, VA 23233

PRINCIPAL DISPLAY PANEL - 473 mL Bottle Label

NDC 68599-2302-6

McKESSON

Isopropyl Rubbing Alcohol 70%

USP | FIRST AID ANTISEPTIC

16FL OZ (1 PT)
(473 mL)

TAMPER EVIDENT CAP FOR YOUR PROTECTION.
IF RING-BAND IS DETACHED FROM CAP OR MISSING
DO NOT USE.

WARNING:
FLAMMABLE

MFR # 23-D0022

Distributed By McKesson Medical-Surgical Inc.
Richmond, VA 23233
Made in USA

Drug Facts